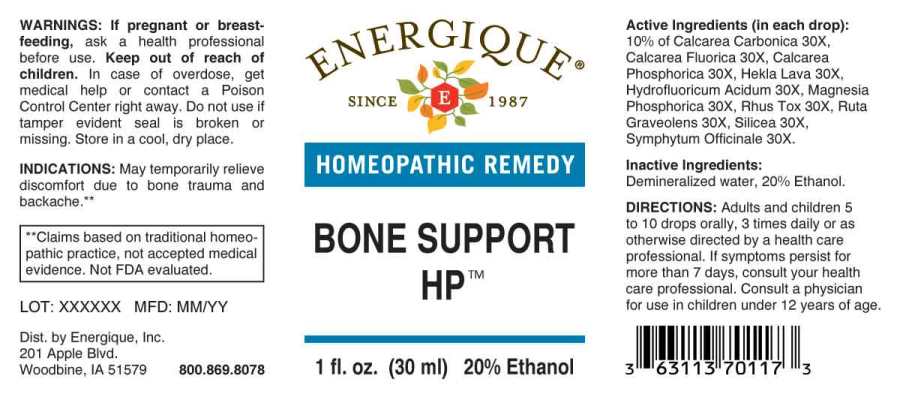 DRUG LABEL: Bone Support
NDC: 44911-0627 | Form: LIQUID
Manufacturer: Energique, Inc.
Category: homeopathic | Type: HUMAN OTC DRUG LABEL
Date: 20221109

ACTIVE INGREDIENTS: OYSTER SHELL CALCIUM CARBONATE, CRUDE 30 [hp_X]/1 mL; CALCIUM FLUORIDE 30 [hp_X]/1 mL; TRIBASIC CALCIUM PHOSPHATE 30 [hp_X]/1 mL; HEKLA LAVA 30 [hp_X]/1 mL; HYDROFLUORIC ACID 30 [hp_X]/1 mL; MAGNESIUM PHOSPHATE, DIBASIC TRIHYDRATE 30 [hp_X]/1 mL; TOXICODENDRON PUBESCENS LEAF 30 [hp_X]/1 mL; RUTA GRAVEOLENS FLOWERING TOP 30 [hp_X]/1 mL; SILICON DIOXIDE 30 [hp_X]/1 mL; COMFREY ROOT 30 [hp_X]/1 mL
INACTIVE INGREDIENTS: WATER; ALCOHOL

Drug Facts:

ACTIVE INGREDIENTS:

(in each drop): 10% of Calcarea Carbonica 30X, Calcarea Fluorica 30X, Calcarea Phosphorica 30X, Hekla Lava 30X, Hydrofluoricum Acidum 30X, Magnesia Phosphorica 30X, Rhus Tox 30X, Ruta Graveolens 30X, Silicea 30X, Symphytum Officinale 30X.

INDICATIONS:

May temporarily relieve discomfort due to bone trauma and backache.**

**Claims based on traditional homeopathic practice, not accepted medical evidence. Not FDA evaluated.

WARNINGS:

If pregnant or breast-feeding, ask a health professional before use.

Keep out of reach of children. In case of overdose, get medical help or contact a Poison Control Center right away.

Do not use if tamper evident seal is broken or missing. Store in a cool, dry place.

DIRECTIONS:

Adults and children 5 to 10 drops orally, 3 times daily or as otherwise directed by a health care professional. If symptoms persist for more than 7 days, consult your health care professional. Consult a physician for use in children under 12 years of age.

INACTIVE INGREDIENTS:

Demineralized Water, 20% Ethanol.

Keep out of reach of children. In case of overdose, get medical help or contact a Poison Control Center right away.

INDICATIONS:

May temporarily relieve discomfort due to bone trauma and backache.**

**Claims based on traditional homeopathic practice, not accepted medical evidence. Not FDA evaluated.

QUESTIONS:

Dist. by Energique, Inc.

201 Apple Blvd

Woodbine, IA 51579 800.869.8078

PACKAGE LABEL DISPLAY:

ENERGIQUE

SINCE 1987

HOMEOPATHIC REMEDY

BONE SUPPORT HP

1 fl. oz. (30 ml)